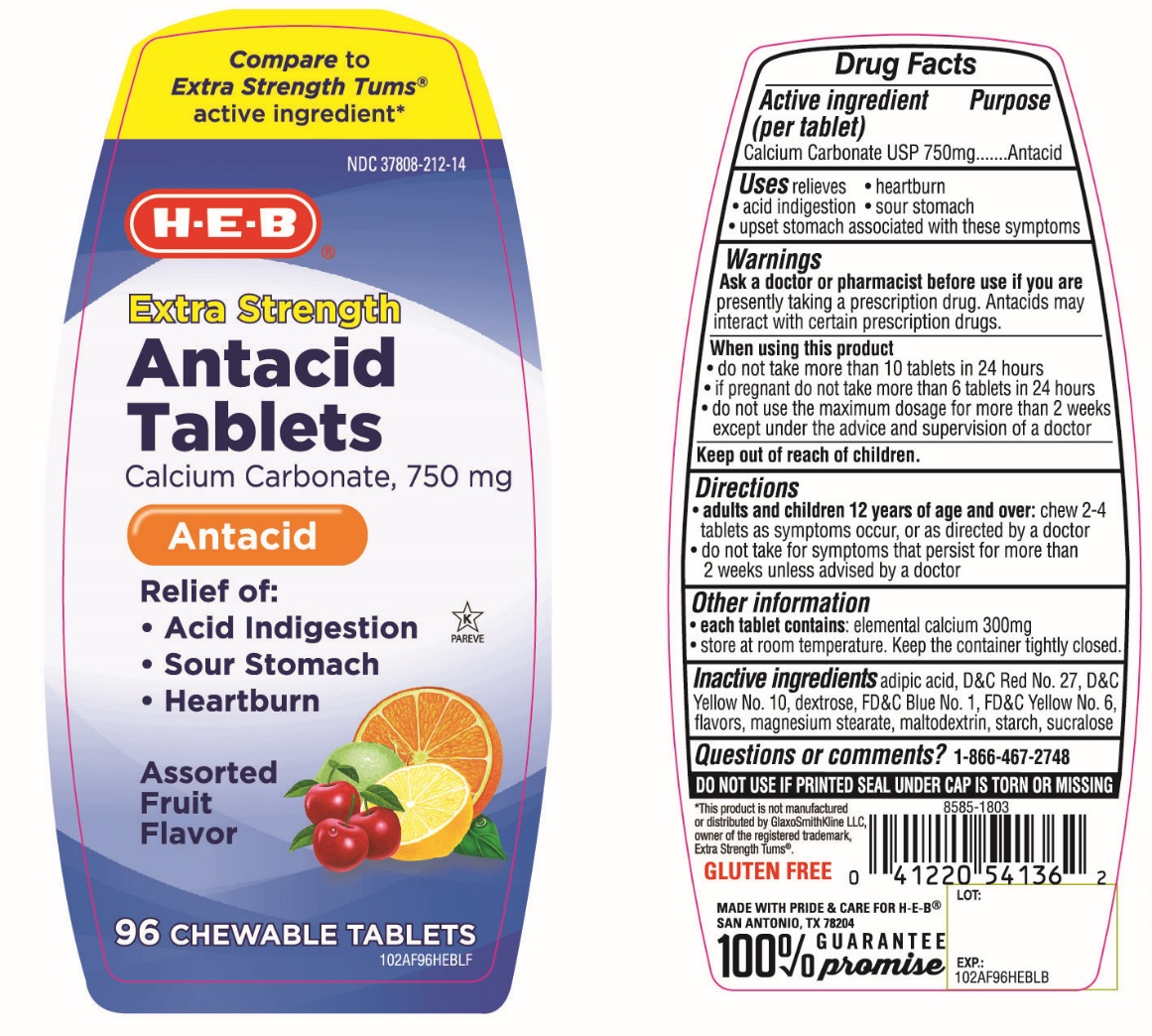 DRUG LABEL: HEB Extra Strength Antacid

NDC: 37808-212 | Form: TABLET, CHEWABLE
Manufacturer: H-E-B
Category: otc | Type: HUMAN OTC DRUG LABEL
Date: 20251003

ACTIVE INGREDIENTS: CALCIUM CARBONATE 750 mg/1 1
INACTIVE INGREDIENTS: ADIPIC ACID; D&C RED NO. 27; D&C YELLOW NO. 10; DEXTROSE, UNSPECIFIED FORM; FD&C BLUE NO. 1; FD&C YELLOW NO. 6; MAGNESIUM STEARATE; MALTODEXTRIN; STARCH, CORN; SUCRALOSE

HEB Extra Strength Antacid Calcium Carbonate Chewable Tablets

Active ingredient (per tablet)

Calcium Carbonate USP 750mg

Purpose

Antacid

Uses

relieves

• heartburn

• acid indigestion

• sour stomach

• upset stomach associated with these symptoms

Warnings

Ask a doctor or pharmacist before use if you arepresently taking a prescription drug. Antacids may interact with certain prescription drugs.

When using this product

- do not take more than 10 tablets in 24 hours
- If pregnant do not take more than 6 tablets in 24 hours
- do not use the maximum dosage for more than 2 weeks except under the advice and supervision of a doctor

Directions

- adults and children 12 years of age and over:chew 2-4 tablets as symptoms occur, or as directed by a doctor
- do not take for symptoms that persist for more than 2 weeks unless advised by a doctor

Other information

- each tablet contains:elemental calcium 300 mg
- store at room temperature. Keep the container tightly closed.

Inactive ingredients

adipic acid, D&C Red No. 27, D&C Yellow 10, dextrose, FD&C Blue No. 1, FD&C Yellow No. 6, flavors, magnesium stearate, maltodextrin, starch, sucralose.

Questions or comments?

1-866-467-2748

SAFETY SEALED: DO NOT USE IF PRINTED SEAL UNDER CAP IS TORN OR MISSING

Package/Label Principal Display Panel

NDC 37808-212-14

H-E-B®

Compare to Extra Strength Tums® active ingredient*

Extra strength

Antacid Tablets

Calcium Carbonate 750 mg

Antacid

Relief of:

- Acid indigestion
- Sour stomach
- Heartburn

Assorted Fruit Flavors

96 CHEWABLE TABLETS

K PAREVE

GLUTEN FREE

100% GUARANTEE promise

MADE WITH PRIDE & CARE FOR H-E-B®SAN ANTONIO, TX 78204

*This product is not manufactured or distributed by GlaxoSmithKline LLC, owner of the registered trademark, Extra Strength Tums®.